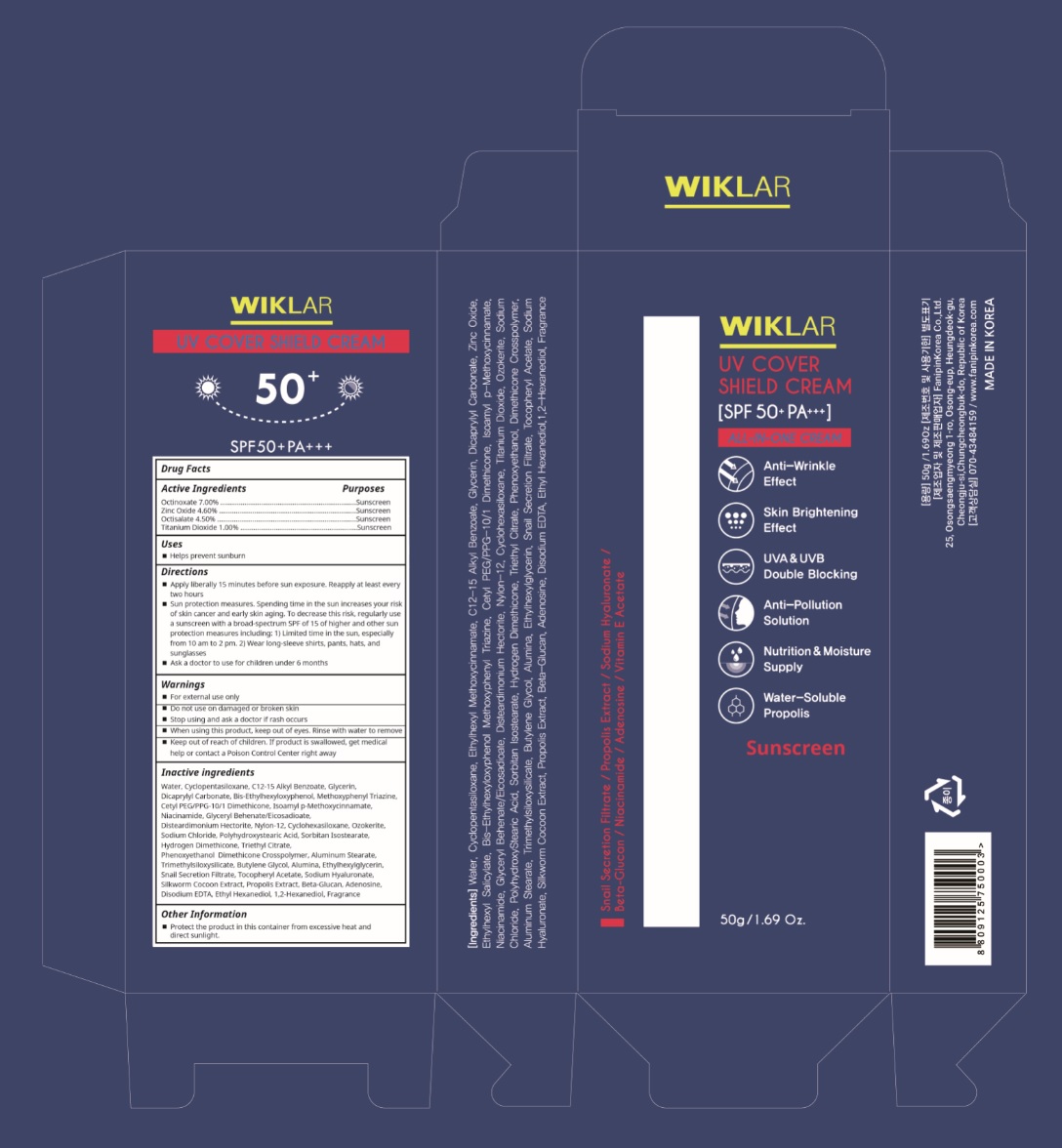 DRUG LABEL: WIKLAR UV COVER SHIELD
NDC: 71460-001 | Form: CREAM
Manufacturer: Fanipinkorea Co., Ltd.
Category: otc | Type: HUMAN OTC DRUG LABEL
Date: 20180614

ACTIVE INGREDIENTS: OCTINOXATE 3.5 g/50 g; ZINC OXIDE 2.3 g/50 g; OCTISALATE 2.25 g/50 g; TITANIUM DIOXIDE 0.5 g/50 g
INACTIVE INGREDIENTS: WATER; CYCLOMETHICONE 5; ALKYL (C12-15) BENZOATE; GLYCERIN; DICAPRYLYL CARBONATE; BEMOTRIZINOL; CETYL PEG/PPG-10/1 DIMETHICONE (HLB 3); AMILOXATE; NIACINAMIDE; GLYCERYL BEHENATE/EICOSADIOATE; DISTEARDIMONIUM HECTORITE; NYLON-12; CYCLOMETHICONE 6; CERESIN; SODIUM CHLORIDE; POLYHYDROXYSTEARIC ACID (2300 MW); SORBITAN ISOSTEARATE; HYDROGEN DIMETHICONE (20 CST); TRIETHYL CITRATE; PHENOXYETHANOL; DIMETHICONE CROSSPOLYMER (450000 MPA.S AT 12% IN CYCLOPENTASILOXANE); ALUMINUM STEARATE; TRIMETHYLSILOXYSILICATE (M/Q 0.6-0.8); BUTYLENE GLYCOL; ALUMINUM OXIDE; ETHYLHEXYLGLYCERIN; .ALPHA.-TOCOPHEROL ACETATE; HYALURONATE SODIUM; BOMBYX MORI FIBER; PROPOLIS WAX; ADENOSINE; EDETATE DISODIUM; ETHOHEXADIOL; 1,2-HEXANEDIOL

Drug Facts

ACTIVE INGREDIENT

Octinoxate 7.00%

Zinc Oxide 4.6%
Octisalate 4.50%
Titanium Dioxide 1.00%

PURPOSE

Sunscreen

INDICATIONS AND USAGE

Helps prevent sunburn

DOSAGE AND ADMINISTRATION

Apply liberally 15 minutes before sun exposure.

Reapply at least every two hours

Sun protection measures. Spending time in the sun increases your risk of skin cancer and early skin aging. To decrease this risk, regularly use a sunscreen with a broad spectrum SPF of 15 of higher and other sun protection measures including: 1) Limited time in the sun, especially from 10 am to 2 pm. 2) Wear long-sleeve shirts, pants, hats, and sunglasses
Ask a doctor to use for children under 6 months

WARNINGS

For external use only.
Do not use on damaged or broken skin.
When using this product, keep out of eyes. Rinse with water to remove.
Stop using and ask a doctor if rash occurs.

KEEP OUT OF REACH OF CHILDREN

Keep out of reach of the children. If product is swallowed, get medical help or contact a poison control center right away.

INACTIVE INGREDIENT

Water, Cyclopentasiloxane, C12-15 Alkyl Benzoate, Glycerin, Dicaprylyl Carbonate, Bis-Ethylhexyloxyphenol, Methoxyphenyl Triazine, Cetyl PEG/PPG-10/1 Dimethicone, Isoamyl p-Methoxycinnamate, Niacinamide, Glyceryl Behenate/Eicosadioate, Disteardimonium Hectorite, Nylon-12, Cyclohexasiloxane, Ozokerite, Sodium Chloride, Polyhydroxystearic Acid, Sorbitan Isostearate, Hydrogen Dimethicone, Triethyl Citrate, Phenoxyethanol
Dimethicone Crosspolymer, Aluminum Stearate, Trimethylsiloxysilicate, Butylene Glycol, Alumina, Ethylhexylglycerin, Snail Secretion Filtrate, Tocopheryl Acetate, Sodium Hyaluronate, Silkworm Cocoon Extract, Propolis Extract, Beta-Glucan, Adenosine, Disodium EDTA, Ethyl Hexanediol, 1,2-Hexanediol, Fragrance